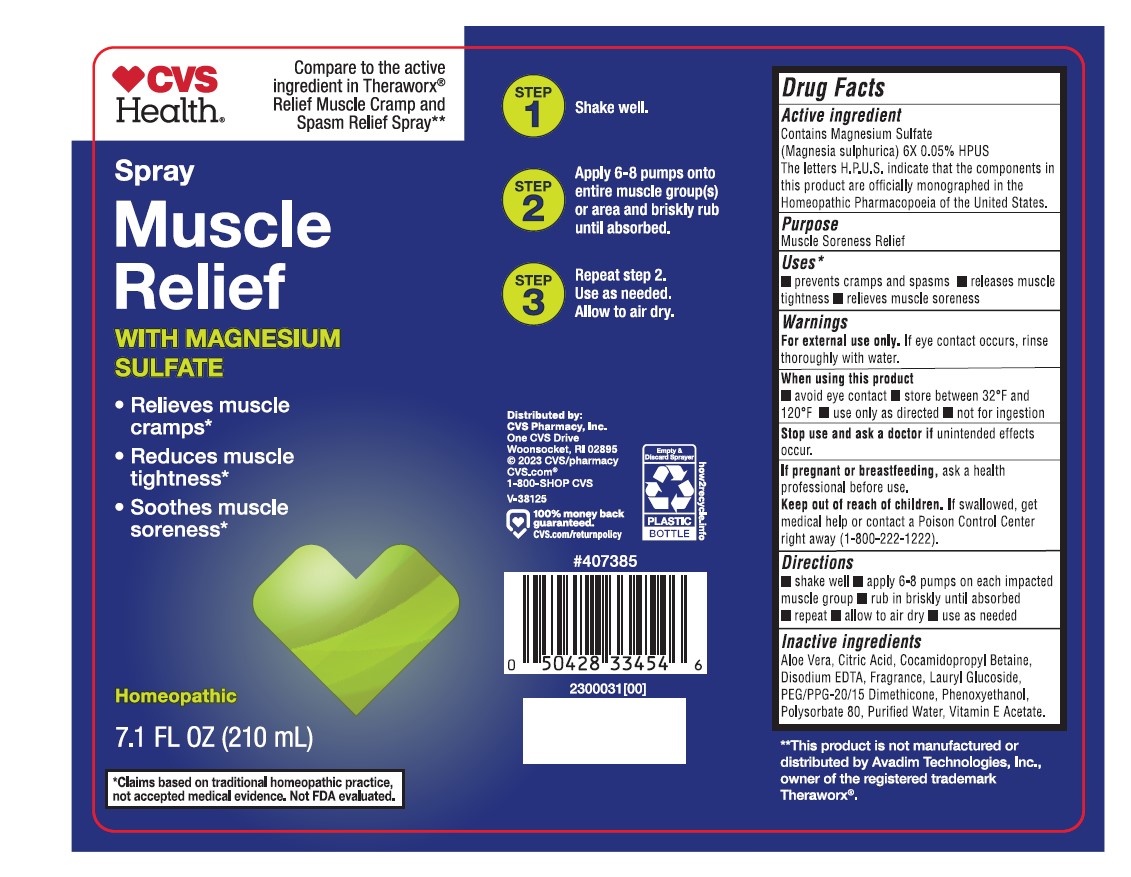 DRUG LABEL: CVS muscle relief
NDC: 51316-143 | Form: SPRAY
Manufacturer: CVS Health
Category: homeopathic | Type: HUMAN OTC DRUG LABEL
Date: 20241211

ACTIVE INGREDIENTS: MAGNESIUM SULFATE HEPTAHYDRATE 6 [hp_X]/210 mL
INACTIVE INGREDIENTS: .ALPHA.-TOCOPHEROL ACETATE; PHENOXYETHANOL; ANHYDROUS CITRIC ACID; LAURYL GLUCOSIDE; EDETATE DISODIUM; COCAMIDOPROPYL BETAINE; ALOE VERA LEAF; WATER; PEG/PPG-20/15 DIMETHICONE; POLYSORBATE 80

CVS muscle relief Spray

ACTIVE INGREDIENT

Contains Magnesium Sulfate (Magnesium sulphurica) 6X 0.05 % HPUS

The letters H.P.U.S indicate that the components in this product are officially monographed in Homeopathic Pharmacopeia of the Unites States.

PURPOSE

Muscle Soreness Relief

INDICATIONS AND USAGE

- prevents cramps and spasms
- releases muscle tightness
- relieves muscle soreness

WARNINGS

For external use only.

If eye contact occurs, rinse thoroughly with water

WHEN USING

avoid eye contact

store between 32°F and 120°F

Use only as directed

not for ingestion

Stop use and ask a doctor if unintended effects occur.

PREGNANCY OR BREAST FEEDING

If pregnant or breastfeeding, ask a health professional before use.

KEEP OUT OF REACH OF CHILDREN

If swallowed, get medical help or contact a Poison Control Center right away (1-800-222-1222).

DOSAGE AND ADMINISTRATION

Shake well

apply 6-8 pumps on each impacted muscle group

rub in briskly until absorbed

repeat

allow to air dry

use as needed

INACTIVE INGREDIENT

Aloe Vera, Citric Acid, Cocamidopropyl Betaine, Disodium EDTA, Fragrance, Lauryl Glucoside, PEG/PPG-20/15 Dimethicone, Phenoxyethanol, Polysorbate 80, Purified Water, Vitamin E Acetate.